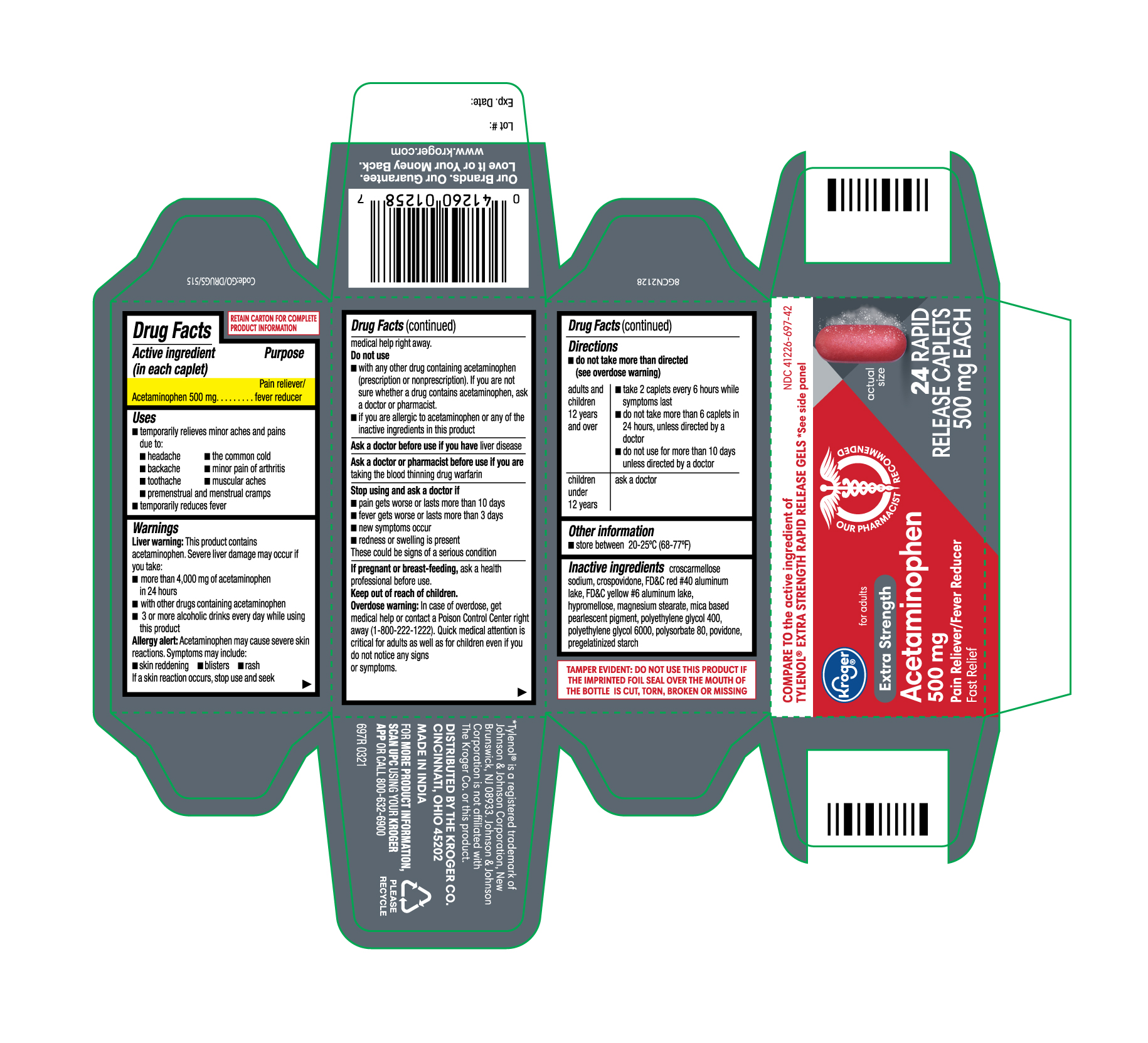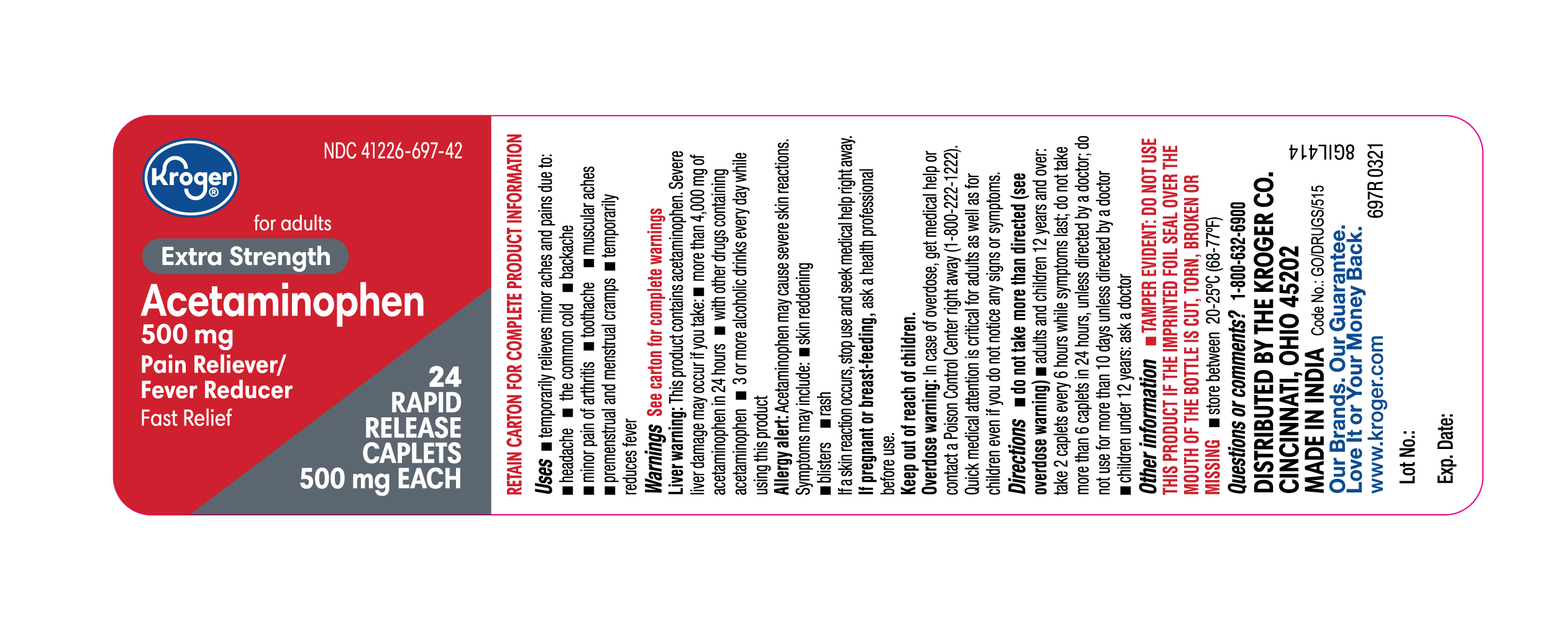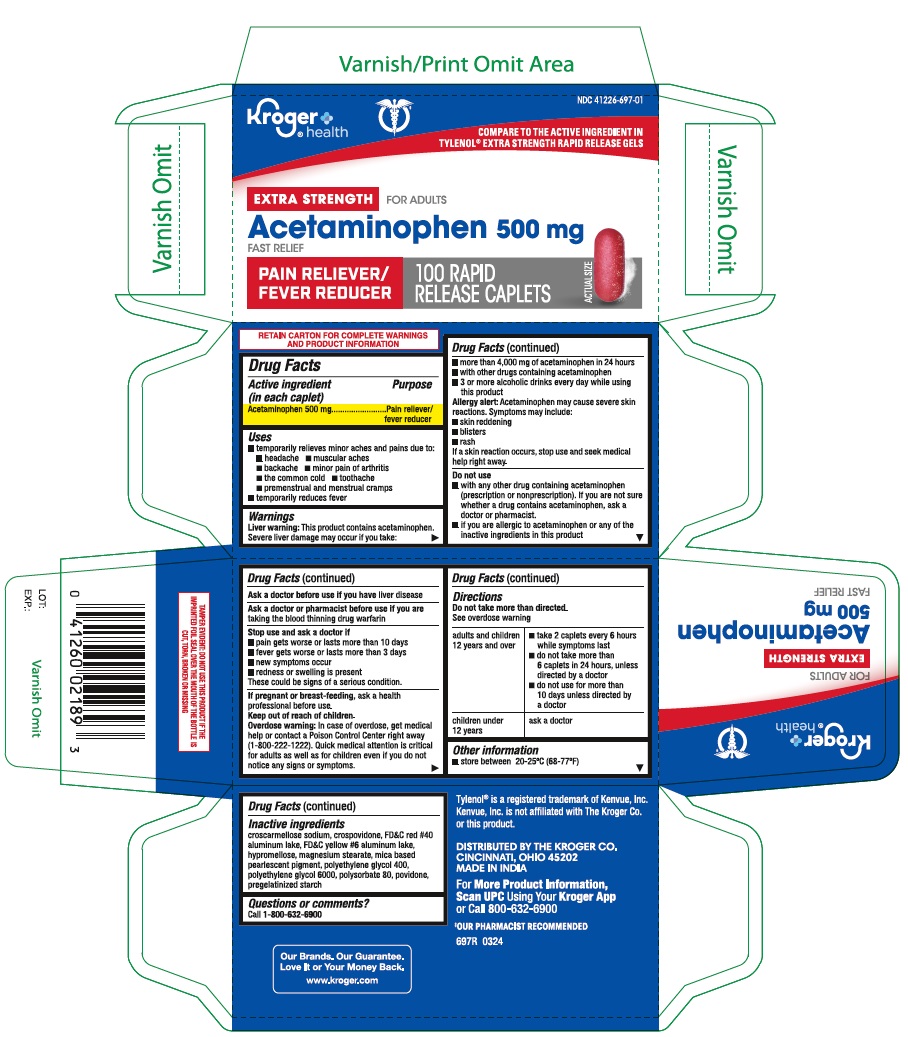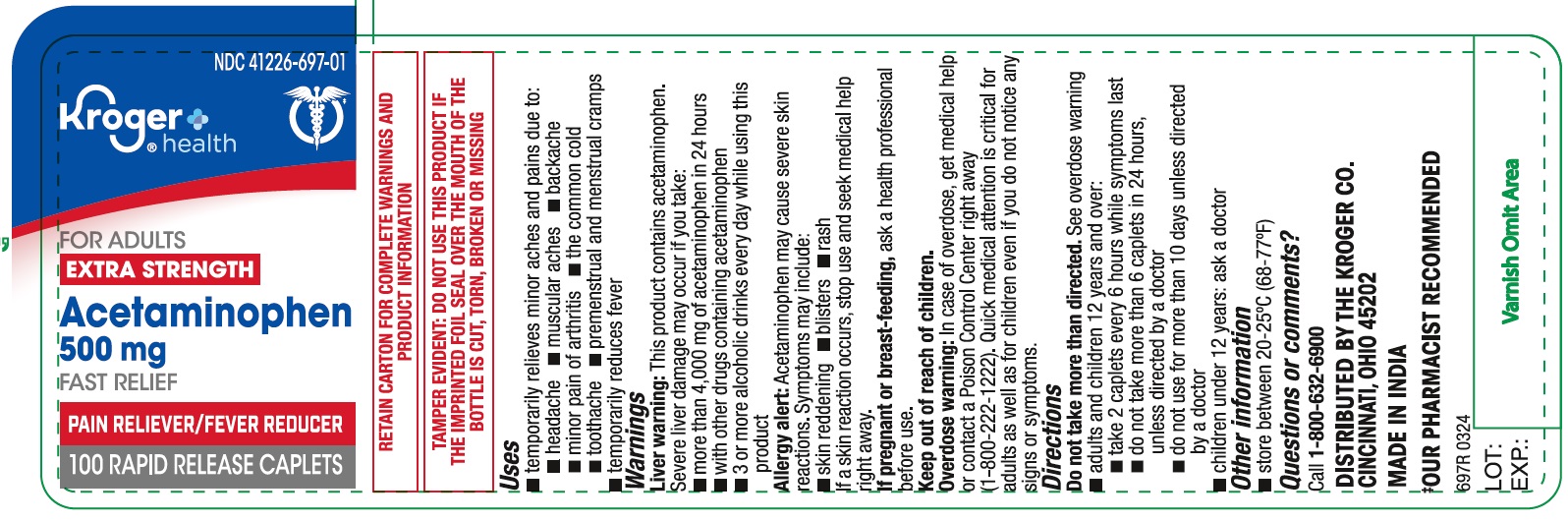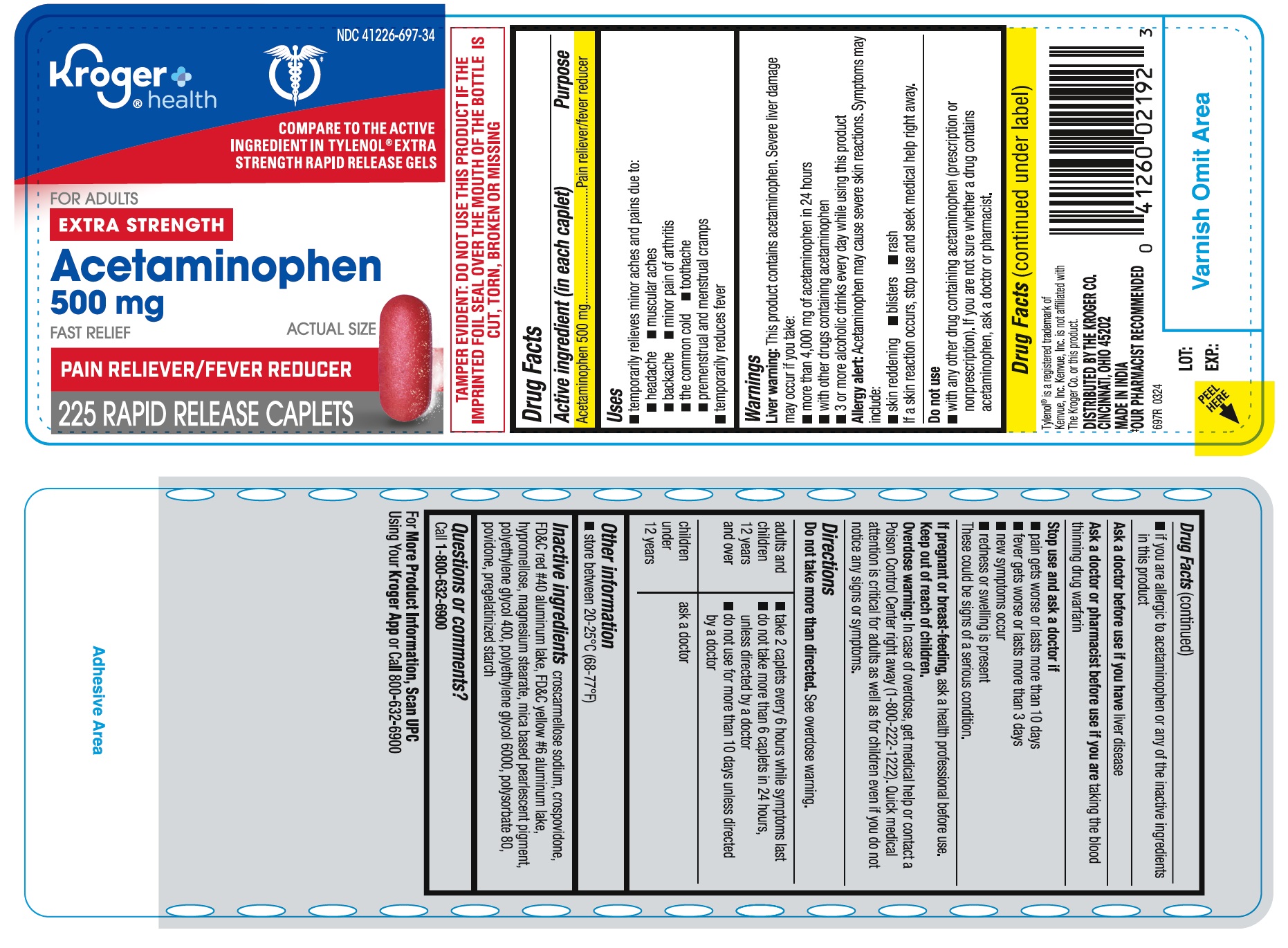 DRUG LABEL: ACETAMINOPHEN
NDC: 41226-697 | Form: TABLET, COATED
Manufacturer: Kroger Company
Category: otc | Type: HUMAN OTC DRUG LABEL
Date: 20240413

ACTIVE INGREDIENTS: ACETAMINOPHEN 500 mg/1 1
INACTIVE INGREDIENTS: POVIDONE K30; STARCH, CORN; MICA; POLYETHYLENE GLYCOL 400; FD&C RED NO. 40; FD&C YELLOW NO. 6; HYPROMELLOSE 2910 (6 MPA.S); MAGNESIUM STEARATE; POLYSORBATE 80; CROSPOVIDONE; POLYETHYLENE GLYCOL 6000; CROSCARMELLOSE SODIUM

Kroger Extra Strength Acetaminophen Rapid Release Tablets

Drug Facts

Acetaminophen 500 mg

ACTIVE INGREDIENT

Acetaminophen 500 mg

PURPOSE

Pain reliever/fever reducer

Uses

temporarily relieves minor aches and pains due to:

- headache
- muscular aches
- backache
- minor pain of arthritis
- the common cold
- toothache
- premenstrual and menstrual cramps

temporarily reduces fever

Warnings
Liver warning: This product contains acetaminophen. Severe liver damage may occur if you take:
•more than 4,000 mg of acetaminophen in 24 hours
•with other drugs containing acetaminophen
•3 or more alcoholic drinks every day while using this product

Allergy alert: acetaminophen may cause severe skin reactions. Symptoms may include:
•skin reddening
•blisters
•rash
If a skin reaction occurs, stop use and seek medical help right away.

Do not use
•with any other drug containing acetaminophen (prescription or nonprescription). If you are not sure whether a drug contains acetaminophen, ask a doctor or pharmacist.
•if you are allergic to acetaminophen or any of the inactive ingredients in this product

Ask a doctor before use if you have liver disease

Ask a doctor or pharmacist before use if you are taking the blood thinning drug warfarin

Stop use and ask a doctor if
•pain gets worse or lasts more than 10 days
•fever gets worse or lasts more than 3 days
•new symptoms occur
•redness or swelling is present
These could be signs of a serious condition.

PREGNANCY OR BREAST FEEDING

If pregnant or breast-feeding, ask a health professional before use.

Keep out of reach of children.
Overdose warning: In case of overdose, get medical help or contact a Poison Control Center right away (1-800-222-1222). Quick medical attention is critical for adults as well as for children even if you do not notice any signs or symptoms.

Directions

- do not take more than directed (see overdose warning)

adults and children 12 years and over

- take 2 caplets every 6 hours while symptoms last
- do not take more than 6 caplets in 24 hours, unless directed by a doctor
- do not use for more than 10 days unless directed by a doctor

children under 12 years

- ask a doctor

OTHER INFORMATION

- store between 20-25°C (68-77°F)

INACTIVE INGREDIENT

Inactive ingredients croscarmellose sodium, crospovidone, FD&C red #40 aluminum lake, FD&C yellow #6 aluminum lake, hypromellose, magnesium stearate, mica based pearlescent pigment, polyethylene glycol 400, polyethylene glycol 6000, polysorbate 80, povidone, pregelatinized starch

Questions or comments? Call 1-800-632-6900